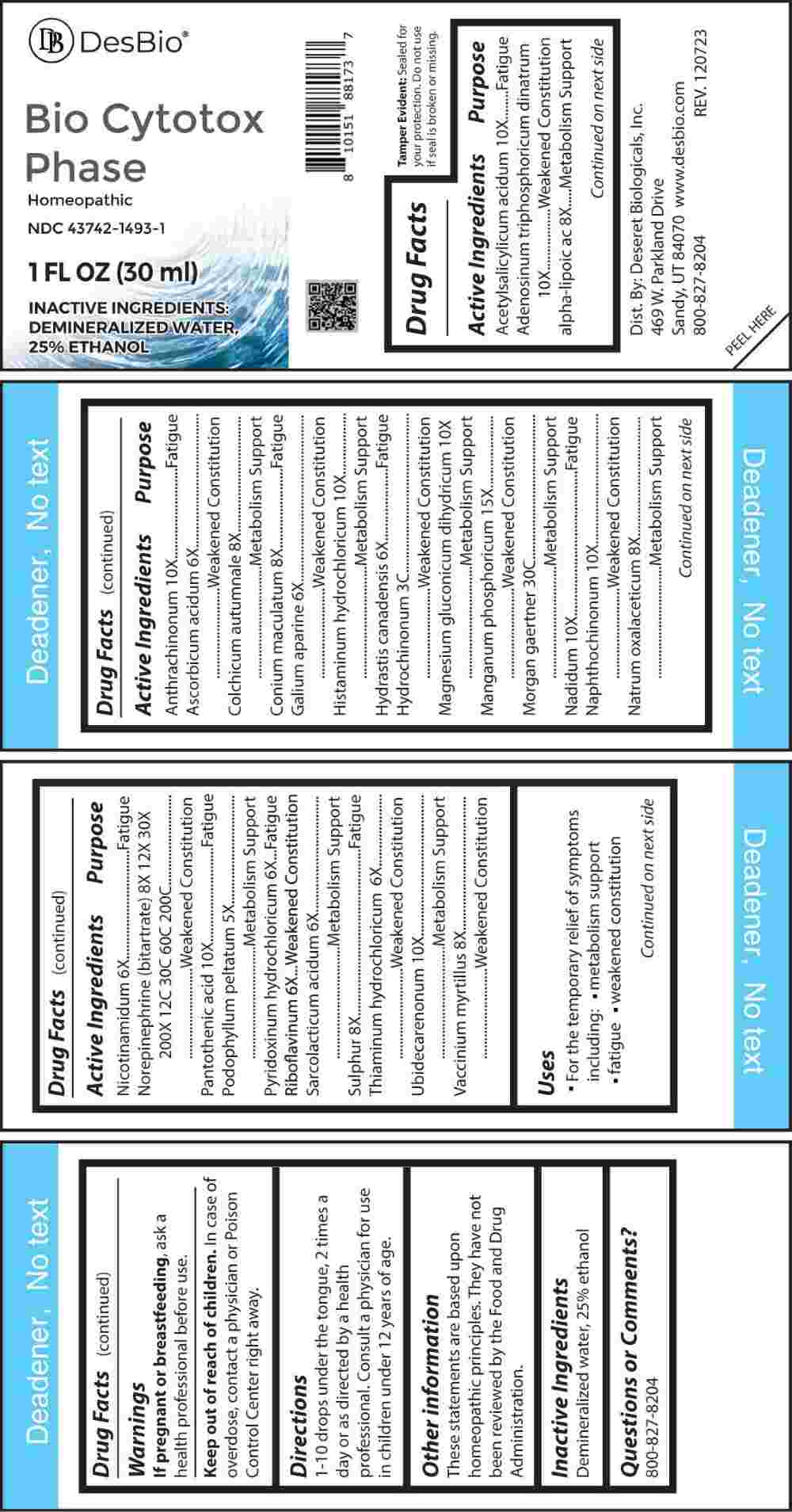 DRUG LABEL: Bio Cytotox Phase
NDC: 43742-1493 | Form: LIQUID
Manufacturer: Deseret Biologicals, Inc.
Category: homeopathic | Type: HUMAN OTC DRUG LABEL
Date: 20240314

ACTIVE INGREDIENTS: PODOPHYLLUM 5 [hp_X]/1 mL; ASCORBIC ACID 6 [hp_X]/1 mL; GALIUM APARINE 6 [hp_X]/1 mL; GOLDENSEAL 6 [hp_X]/1 mL; NIACINAMIDE 6 [hp_X]/1 mL; PYRIDOXINE HYDROCHLORIDE 6 [hp_X]/1 mL; RIBOFLAVIN 6 [hp_X]/1 mL; LACTIC ACID, L- 6 [hp_X]/1 mL; THIAMINE HYDROCHLORIDE 6 [hp_X]/1 mL; THIOCTIC ACID 8 [hp_X]/1 mL; COLCHICUM AUTUMNALE BULB 8 [hp_X]/1 mL; CONIUM MACULATUM FLOWERING TOP 8 [hp_X]/1 mL; SODIUM DIETHYL OXALACETATE 8 [hp_X]/1 mL; SULFUR 8 [hp_X]/1 mL; BILBERRY 8 [hp_X]/1 mL; NOREPINEPHRINE BITARTRATE 10 [hp_X]/1 mL; ASPIRIN 10 [hp_X]/1 mL; ADENOSINE TRIPHOSPHATE DISODIUM 10 [hp_X]/1 mL; ANTHRAQUINONE 10 [hp_X]/1 mL; HISTAMINE DIHYDROCHLORIDE 10 [hp_X]/1 mL; MAGNESIUM GLUCONATE 10 [hp_X]/1 mL; NADIDE 10 [hp_X]/1 mL; NAPHTHOQUINE 10 [hp_X]/1 mL; UBIDECARENONE 10 [hp_X]/1 mL; PANTOTHENIC ACID 10 [hp_X]/1 mL; MANGANESE PHOSPHATE, DIBASIC 15 [hp_X]/1 mL; HYDROQUINONE 3 [hp_C]/1 mL; SALMONELLA ENTERICA SUBSP. ENTERICA SEROVAR ENTERITIDIS 30 [hp_C]/1 mL
INACTIVE INGREDIENTS: WATER; ALCOHOL

DRUG FACTS:

ACTIVE INGREDIENTS:

Acetylsalicylicum Acidum 10X, Adenosinum Triphosphoricum Dinatrum 10X, Alpha-Lipoicum Acidum 8X, Anthrachinonum 10X, Ascorbicum Acidum 6X, Colchicum Autumnale 8X, Conium Maculatum 8X, Galium Aparine 6X, Histaminum Hydrochloricum 10X, Hydrastis Canadensis 6X, Hydrochinonum 3C, Magnesium Gluconate Dihydricum 10X, Manganum Phosphoricum 15X, Morgan Gaertner 30C, Nadidum 10X, Naphthochinonum 10X, Natrum Oxalaceticum 8X, Nicotinamidum 6X, Norepinephrine (Bitartrate) 8X, 12X, 30X, 200X, 12C, 30C, 60C, 200C, Pantothenic Acid 10X, Podophyllum Peltatum 5X, Pyridoxinum Hydrochloricum 6X, Riboflavinum 6X, Sarcolacticum Acidum 6X, Sulphur 8X, Thiaminum Hydrochloricum 6X, Ubidecarenonum 10X, Vaccinium Myrtillus 8X

PURPOSE:

Acetylsalicylicum Acidum - Fatigue, Adenosinum Triphosphoricum Dinatrum – Weakened Constitution, Alpha-Lipoicum Acidum – Metabolism Support, Anthrachinonum - Fatigue, Ascorbicum Acidum – Weakened Constitution, Colchicum Autumnale – Metabolism Support, Conium Maculatum - Fatigue, Galium Aparine – Weakened Constitution, Histaminum Hydrochloricum – Metabolism Support, Hydrastis Canadensis - Fatigue, Hydrochinonum – Weakened Constitution, Magnesium Gluconate Dihydricum – Metabolism Support, Manganum Phosphoricum – Weakened Constitution, Morgan Gaertner – Metabolism Support, Nadidum - Fatigue, Naphthochinonum – Weakened Constitution, Natrum Oxalaceticum – Metabolism Support, Nicotinamidum - Fatigue, Norepinephrine (Bitartrate) – Weakened Constitution, Pantothenic Acid - Fatigue, Podophyllum Peltatum – Metabolism Support, Pyridoxinum Hydrochloricum - Fatigue, Riboflavinum – Weakened Constitution, Sarcolacticum Acidum – Metabolism Support, Sulphur - Fatigue, Thiaminum Hydrochloricum – Weakened Constitution, Ubidecarenonum – Metabolism Support, Vaccinium Myrtillus – Weakened Constitution

USES:

• For the temporary relief of symptoms including:

• metabolism support • fatigue • weakened constitution

These statements are based upon homeopathic principles. They have not been reviewed by the Food and Drug Administration.

WARNINGS:

If pregnant of breast-feeding, ask a health professional before use.

Keep out of reach of children. In case of overdose, contact a physician or Poison Control Center right away.

Tamper Evident: Sealed for your protection. Do not use if seal is broken or missing.

KEEP OUT OF REACH OF CHILDREN:

In case of overdose, contact a physician or Poison Control Center right away.

DIRECTIONS:

1-10 drops under the tongue, 2 times a day or as directed by a health professional. Consult a physician for use in children under 12 years of age.

INACTIVE INGREDIENTS:

Demineralized water, 25% ethanol

QUESTIONS:

Dist. By: Deseret Biologicals, Inc.

469 W. Parkland Drive

Sandy, UT 84070

www.desbio.com

800-827-8204

PACKAGE LABEL DISPLAY:

Des Bio

Bio Cytotox

Phase

Homeopathic
NDC 43742-1493-1
1 FL OZ (30 ml)